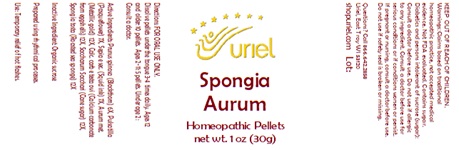 DRUG LABEL: Spongia Aurum
NDC: 48951-8201 | Form: PELLET
Manufacturer: Uriel Pharmacy Inc.
Category: homeopathic | Type: HUMAN OTC DRUG LABEL
Date: 20251107

ACTIVE INGREDIENTS: PRUNUS SPINOSA FLOWER BUD 6 [hp_X]/1 1; PULSATILLA VULGARIS 7 [hp_X]/1 1; SEPIA OFFICINALIS JUICE 7 [hp_X]/1 1; GOLD 12 [hp_X]/1 1; CALCIUM CARBONATE 12 [hp_X]/1 1; SUGARCANE 12 [hp_X]/1 1; SPONGIA OFFICINALIS SKELETON, ROASTED 12 [hp_X]/1 1
INACTIVE INGREDIENTS: SUCROSE

Spongia Aurum

INDICATIONS AND USAGE

Directions: FOR ORAL USE ONLY.

DOSAGE AND ADMINISTRATION

Dissolve pellets under the tongue 3-4 times daily. Ages 12 and older: 10 pellets. Ages 2-11: 5 pellets. Under age 2: Consult a doctor.

ACTIVE INGREDIENT

Active Ingredients: Prunus spinosa (Blackthorn) 6X, Pulsatilla (Pasqueflower) 7X, Sepia e sec. (Squid ink) 7X, Aurum met. (Metallic gold) 12X, Calc. carb e testa ovi (Calcium carbonate from eggshells) 12X, Saccharum Sacchari (Cane sugar) 12X, Spongia tosta (Roasted sea sponge) 12X

Inactive Ingredient: Organic sucrose

Prepared using rhythmical processes.

PURPOSE

Use: Temporary relief of hot flashes.

KEEP OUT OF REACH OF CHILDREN.

WARNINGS

Warnings: Claims based on traditional homeopathic practice, not accepted medical evidence. Not FDA evaluated. Contains sugar. Diabetics and persons intolerant of sucrose (sugar): Consult a doctor before use. Do not use if allergic to any ingredient. Consult a doctor before use for serious conditions or if conditions worsen or persist. If pregnant or nursing, consult a doctor before use. Do not use if safety seal is broken or missing.

Questions? Call 866.642.2858
Uriel, East Troy WI 53120
shopuriel.com